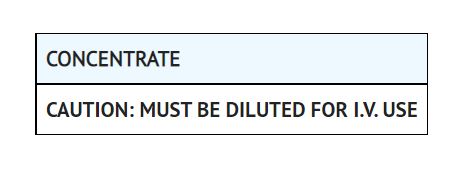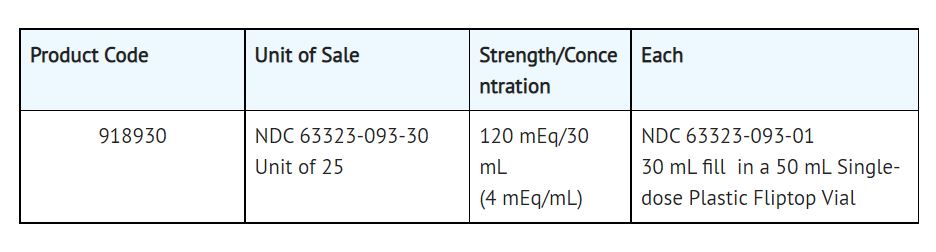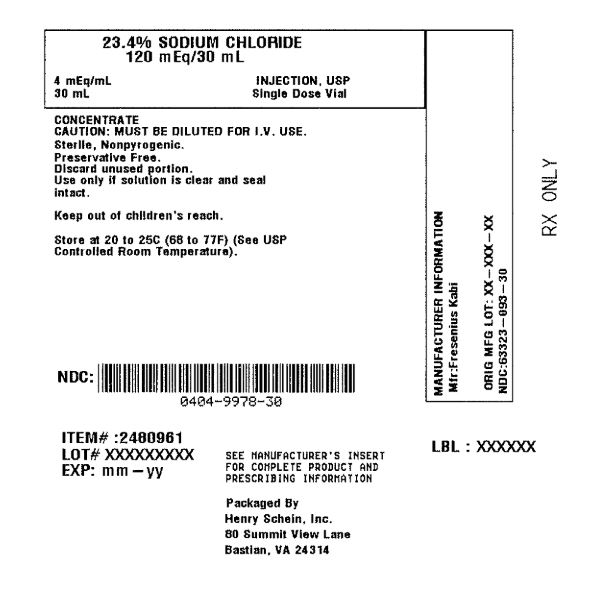 DRUG LABEL: SODIUM CHLORIDE
NDC: 0404-9978 | Form: INJECTION, SOLUTION, CONCENTRATE
Manufacturer: Henry Schein, Inc.
Category: prescription | Type: HUMAN PRESCRIPTION DRUG LABEL
Date: 20251107

ACTIVE INGREDIENTS: SODIUM CHLORIDE 4 meq/1 mL
INACTIVE INGREDIENTS: HYDROCHLORIC ACID; WATER; SODIUM HYDROXIDE

Sodium Chloride

Rx only

8008 mOsmol/L (calc.)
(pH 4.5-7.0 when diluted to a concentration of 0.9%)

Description

Sodium Chloride Injection, USP, 23.4%, is a concentrated, nonisotonic, sterile, nonpyrogenic solution of sodium chloride 234 mg in Water for Injection. pH adjusted with sodium hydroxide or hydrochloric acid if necessary.
Sodium chloride is an electrolyte replenisher. It occurs as colorless cubic crystals or white crystalline powder and has a saline taste. Sodium chloride is freely soluble in water; it is soluble in glycerin and slightly soluble in alcohol.
The empirical formula for sodium chloride is NaCl and the molecular weight is 58.44.

Clinical Pharmacology

Sodium chloride comprises over 90% of the inorganic constituents of the blood serum. Both its ions are physiologically important. Sodium, more than any other ion, determines the osmotic pressure of interstitial fluids and the degree of hydration of tissues. When the intake of the chloride ion is less than is excreted, there is a relative increase in the blood bicarbonate level, producing the condition known as alkalosis. Other symptoms of sodium chloride deficiency are nausea, vomiting and increased irritability of muscles, evidenced by cramps and, possibly, convulsions. It is well known that excessive sweating will cause ‘‘heatcramps,’’ i.e., muscle cramps in the abdomen and extremities, which can be completely relieved only by ingestion of a weak salt solution.
Approximately 25% of the total body sodium is found in the bone. The regulation of salt and water metabolism is governed by different mechanisms; however, changes in the intake, distribution and output of salt are, in health, associated with collateral shifts of water so that electrolyte concentrations are maintained within a narrow range. In the presence of disease affecting the cardiovascular, hepatic or renal system or in certain endocrinologic disorders, changes in the rate of excretion of salt and water will disturb the homeostatic equilibrium. Frequently, abnormalities in the metabolism of water or salt may occur as a result of vomiting, diarrhea, gastrointestinal suction and fever. Excessive sweating will produce loss of water or salt, but since the electrolyte concentration is hypotonic, loss of water will predominate.
The normal salt intake ranges from 5 to 15 grams daily, most of which is excreted by the kidneys. The control of water and salt excretion in urine is very intricate, involving filtration by the glomerulus and reabsorption by the tubules of approximately 99% of the filtered load. The actual quantities excreted depends on the requirements prevailing at the moment. The finer adjustments of the tubular absorptive mechanisms are influenced by osmotic interrelationships between cell water, plasma and urine and by certain steroid hormones influencing electrolyte excretion and the posterior pituitary hormone regulating water excretion. When food intake ceases or salt is withheld, the content of sodium chloride in urine diminishes rapidly so that the body stores are retained. Similar renal retention of electrolytes occurs when salt is lost via gastrointestinal secretion through vomiting, etc. In other conditions, such as congestive heart failure, cirrhosis, nephritis or hypersecretion of the adrenal cortical hormones, the kidney fails to eliminate sufficient sodium. This results in retention of both salt and water, producing an excessive accumulation of extracellular fluid, which may be effectively combated by a sharp restriction of salt intake and use of a diuretic.
Depletion of body salt may be caused in many ways, one of which is too energetic treatment of fluid and sodium retention. Besides this, diabetic acidosis, burns, excessive sweating with free drinking of water, repeated paracentesis for removal of ascitic fluid, adrenal cortical hypofunction and certain forms of nephritis, as well as abnormal losses of gastrointestinal secretions, will cause marked salt depletion. With salt loss, there is a reduction of the osmotic pressure of the extracellular fluid; the urine volume may be retained but it is free of sodium chloride.

Indications and Usage

Sodium Chloride Injection, USP, 23.4%, is indicated as an additive in parenteral fluid therapy for use in patients who have special problems of sodium electrolyte intake or excretion. It is intended to meet the specific requirements of the patient with unusual fluid and electrolyte needs. After available clinical and laboratory information is considered and correlated, the appropriate number of milliequivalents of sodium chloride required can be withdrawn from Sodium Chloride Injection, USP, 23.4% and diluted for use.
Sodium Chloride Injection is indicated for the treatment of sodium, chloride and water deficiencies that commonly occur in many diseases. Isotonic Sodium Chloride Injection should be limited to cases in which the chloride loss is greater than the sodium loss, as in vomiting from pyloric obstruction, or in which the loss is about equal, as in vomiting from duodenal, jejunal or ileal obstruction and in the replacement of aspirated gastrointestinal fluids.
The toxic symptoms that follow various forms of intestinal obstruction are accompanied by a marked reduction of blood chloride and often sodium chloride has a lifesaving effect.
Symptoms of sodium chloride deficiency are very similar to those of Addison’s disease and large doses of sodium chloride will produce temporary alleviation of the symptoms. Other disorders in which sodium chloride is therapeutically useful include extensive burns, failure of gastric secretion and postoperative intestinal paralysis.

Contraindications

Surgical patients should seldom receive salt- containing solutions immediately following surgery unless factors producing salt depletion are present. Because of renal retention of salt during surgery, additional electrolyte given intravenously may result in fluid retention, edema and overloading of the circulation.

Warnings

This product contains aluminum that may be toxic. Aluminum may reach toxic levels with prolonged parenteral administration if kidney function is impaired. Premature neonates are particularly at risk because their kidneys are immature, and they require large amounts of calcium and phosphate solutions, which contain aluminum. Research indicates that patients with impaired kidney function, including premature neonates, who receive parenteral levels of aluminum at greater than 4 to 5 mcg/kg/day accumulate aluminum at levels associated with central nervous system and bone toxicity. Tissue loading may occur at even lower rates of administration.
Sodium Chloride Injection, USP, 23.4% is hypertonic and must be diluted prior to administration. Inadvertent direct injection or absorption of concentrated sodium chloride solution may give rise to sudden hypernatremia and such complications as cardiovascular shock, central nervous system disorders, extensive hemolysis and cortical necrosis of the kidneys.

Precautions

General
Excessive amounts of sodium chloride by any route may cause hypopotassemia and acidosis. Excessive amounts by the parenteral route may precipitate congestive heart failure and acute pulmonary edema, especially in patients with cardiovascular disease and in patients receiving corticosteroids or corticotropin or drugs that may give rise to sodium retention.

Pregnancy
Animal reproduction studies have not been conducted with Sodium Chloride Injection. It is also not known whether Sodium Chloride Injection can cause fetal harm when administered to a pregnant woman or can affect reproduction capacity. Sodium Chloride Injection should be given to a pregnant woman only if clearly needed.

Nursing Mothers
It is not known whether sodium chloride is excreted in human milk. Because many drugs are excreted in human milk, caution should be exercised when Sodium Chloride Injection is administered to a nursing woman.

Use in Children
Safety and effectiveness in children have not been established.

Adverse Reactions

Parenteral administration of quantities of sodium in excess of the amount of water or sodium chloride needed or at a rate more rapid than can be accommodated by the patient’s circulatory function may result in edema and clinical findings resembling those of congestive heart failure. Adverse effects are particularly likely to develop in patients with impaired renal or cardiac function.
Signs of postoperative salt intolerance include cellular dehydration, weakness, disorientation, anorexia, nausea, distention, deep respiration, oliguria and increased blood urea nitrogen.

Overdosage

Administration of too much sodium chloride may result in serious electrolyte disturbances with resulting retention of water, edema, loss of potassium and aggravation of an existing acidosis.

When intake of sodium chloride is excessive, excretion of crystalloids is increased in an attempt to maintain normal osmotic pressure. Thus there is increased excretion of potassium and of bicarbonate and, consequently, a tendency toward acidosis. There is also a rapid elimination of any foreign salt, such as iodide and bromide, being used for therapy.

Dosage and Administration

The dosage of Sodium Chloride Injection, USP, 23.4%, as an additive in parenteral fluid therapy is predicated on specific requirements of the patient after necessary clinical and laboratory information is considered and correlated. The appropriate volume is then withdrawn for proper dilution. Having determined the milliequivalents of sodium chloride to be added, divide by four to calculate the numbers of milliliters (mL) of sodium chloride to be used. Withdraw this volume aseptically and transfer the additive solution into appropriate intravenous solutions such as 5% Dextrose Injection. The properly diluted solutions may be given intravenously.
Parenteral drug products should be inspected visually for particulate matter and discoloration prior to administration, whenever solution and container permit.

How Supplied

Sodium Chloride Injection, USP, 23.4% is supplied as follows:

Store at 20° to 25°C (68° to 77°F) [See USP Controlled Room Temperature]. Preservative Free. Discard unused portion.
Use only if solution is clear and seal intact.

The container closure is not made with natural rubber latex.

Product repackaged by: Henry Schein, Inc., Bastian, VA 24314
From Original Manufacturer/Distributor's NDC and Unit of Sale | To Henry Schein Repackaged Product NDC and Unit of Sale | Total Strength/Total Volume (Concentration) per unit
NDC 63323-093-30 30 mL fill in a 50 mL Single-dose Plastic Fliptop Vial Unit of 25 | NDC 0404-9978-30 1 30 mL Single-dose Plastic Fliptop Vial in a bag (Vial bears NDC 63323-093-01) | 23.4% 120 mEq/30 mL (4 mEq/mL)

FRESENIUS KABI

Lake Zurich, IL 66047

www.fresenius-kabi.com/us

451644A
Revised: April 2021